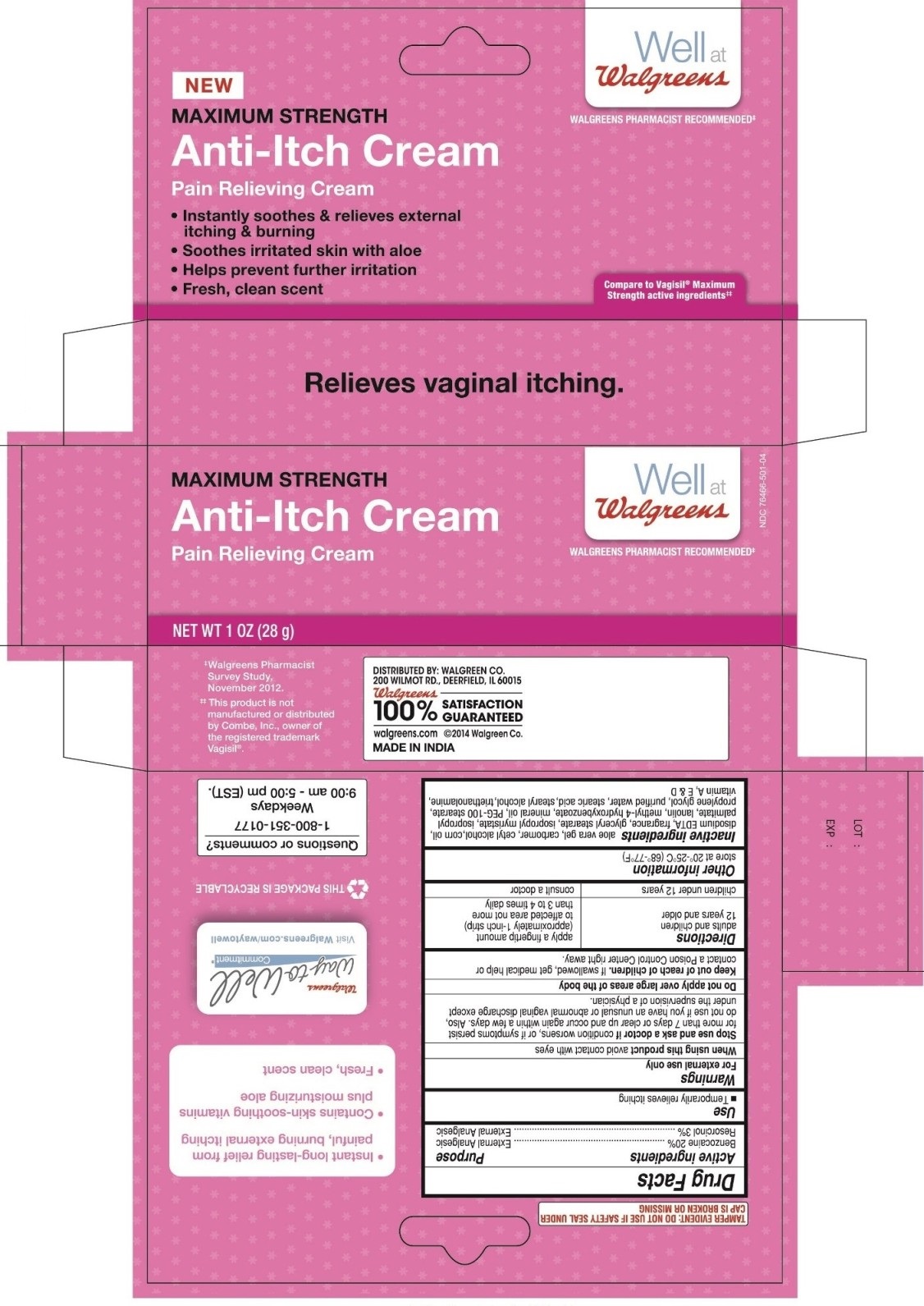 DRUG LABEL: Well at Walgreens Anti-Itch


NDC: 0363-0674 | Form: CREAM
Manufacturer: Walgreens
Category: otc | Type: HUMAN OTC DRUG LABEL
Date: 20220131

ACTIVE INGREDIENTS: BENZOCAINE 20 g/100 g; RESORCINOL 3 g/100 g
INACTIVE INGREDIENTS: ALOE VERA LEAF; CARBOXYPOLYMETHYLENE; CETYL ALCOHOL; CORN OIL; EDETATE DISODIUM; GLYCERYL MONOSTEARATE; ISOPROPYL MYRISTATE; ISOPROPYL PALMITATE; LANOLIN; METHYLPARABEN; MINERAL OIL; PEG-100 STEARATE; PROPYLENE GLYCOL; WATER; STEARIC ACID; STEARYL ALCOHOL; TROLAMINE; VITAMIN A; VITAMIN D; .ALPHA.-TOCOPHEROL

Well at Walgreens Anti-Itch

Active ingredients

Benzocaine 20%

Resorcinol 3%

Purpose

External Analgesic

External Analgesic

Use

- Temporarily relieves itching

Warnings

For external use only

When using this product avoid contact with eyes

Stop use and ask a doctor if condition worsens, or if symptoms persist for more than 7 days or clear up and occur again within a few days. Also, do not use if you have an unusual or abnormal vaginal discharge except under the supervision of a physician.

Do not apply over large areas of the body.

Keep out of reach of children. If swallowed, get medical help or contact a Poison Control Center right away.

Directions

adults and children 12 years and older

apply a fingertip amount (approximately 1-inch strip) to affected area not more than 3 to 4 times daily

children under 12 years

consult a doctor

Other information

store at 20°-25°C (68°-77°F)

Inactive ingredients

aloe vera gel, carbomer, cetyl alcohol, corn oil, disodium EDTA, fragrance, glyceryl stearate, isopropyl myristate, isopropyl palmitate, lanolin, methyl-4 hydroxybenzoate, mineral oil, PEG-100 stearate, propylene glycol, purified water, stearic acid, stearyl alcohol, triethanolamine, vitamin A, E & D

Principal display panel - 28 g Carton Label

Well at Walgreens

WALGREENS PHARMACIST RECOMMENDED‡

NEW

MAXIMUM STRENGTH

Anti-Itch Cream

Pain Relieving Cream

- Instantly soothes & relieves external itching & burning
- Soothes irritated skin with aloe
- Helps prevent further irritation
- Fresh, clean scent

Compared to Vaglsil® Maximum Strength active ingredients‡‡

Relieves vaginal itching.

NDC 0363-0674-64

Well at Walgreens

WALGREENS PHARMACIST RECOMMENDED‡

MAXIMUM STRENGTH

Anti-Itch Cream

Pain Relieving Cream

NET WT 1 OZ (28 g)